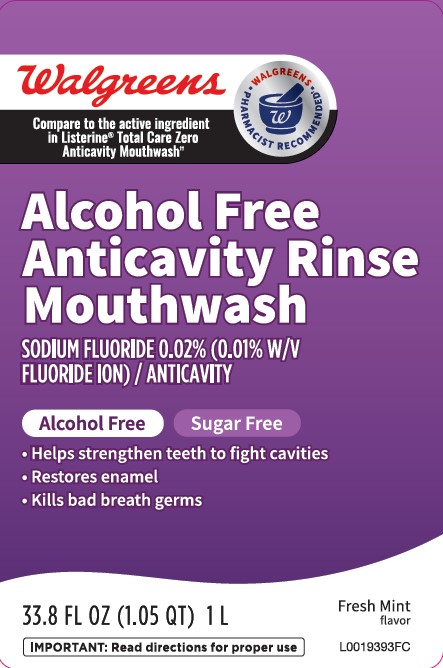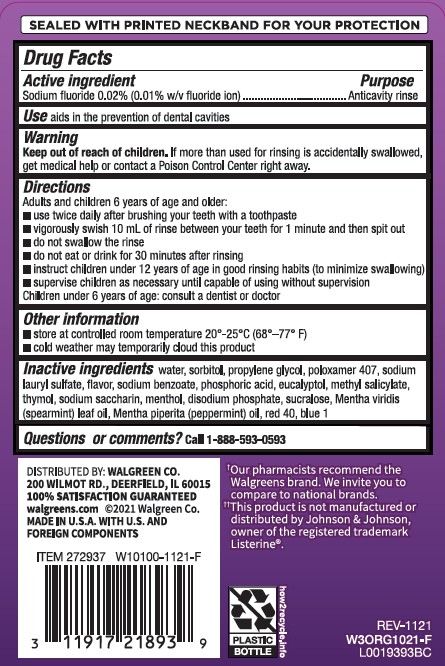 DRUG LABEL: Anticavity
NDC: 0363-0171 | Form: RINSE
Manufacturer: Walgreen Co.
Category: otc | Type: HUMAN OTC DRUG LABEL
Date: 20260212

ACTIVE INGREDIENTS: SODIUM FLUORIDE 0.1 mg/1 mL
INACTIVE INGREDIENTS: WATER; SORBITOL; PROPYLENE GLYCOL; POLOXAMER 407; SODIUM LAURYL SULFATE; SODIUM BENZOATE; PHOSPHORIC ACID; EUCALYPTOL; METHYL SALICYLATE; THYMOL; SACCHARIN SODIUM; MENTHOL; SODIUM PHOSPHATE, DIBASIC, ANHYDROUS; SUCRALOSE; SPEARMINT OIL; PEPPERMINT OIL; FD&C RED NO. 40; FD&C BLUE NO. 1

Walgreens 971.001/971AB
Burn-Free Fluoride Anti-Cavity Mouthwash

Tamper Evident Statement

SEALED WITH PRINTD NECKBAND FOR YOUR PROTCTION

Active Ingredient

Sodium fluoride 0.02% (0.01% w/v fluoride ion)

Purpose

Anticavity rinse

Use

aids in the prevention of dental cavities

Warning

for this product

Keep out of Reach of Children

If more than used for rinsing is accidentally swallowed, get medical help or contact a Poison Control Center right away.

Directions

Adults and children 6 years of age and older:

- use twice daily after brushing your teeth with a toothpaste
- vigorously swish 10 mL of rinse between your teeth for 1 minute and then spit out
- do not swallow the rinse
- do not eat or drink for 30 minutes after rinsing
- instruct children under 12 years of age in good rinsing habits (to minimize swallowing)
- supervise children as necessary until capable of using without supervision

Children under 6 years of age: consult a dentist or doctor

Other information

- store at controlled room temperature 20°-25°C (68°–77° F)
- cold weather may temporarily cloud this product

Inactive ingredients

water, sorbitol, propylene glycol, poloxamer 407, sodium lauryl sulfate, flavor, sodium benzoate, phosphoric acid, eucalyptol, methyl salicylate, thymol, sodium saccharin, menthol, disodium phosphate, sucralose, Mentha viridis (spearmint) leaf oil, Mentha piperita (peppermint) oil, red 40, blue 1

Claims

†Our pharmacists recommend the Walgreens brand. We invite you to compare to national brands.

Disclaimer

††This product is not manufactured or distributed by Johnson & Johnson, owner of the registered trademark Listerine®.

Adverse reactions section

DISTRIBUTED BY: WALGREEN CO.

200 WILMOT RD., DEERFIELD, IL 60015

100% SATISFACTION GUARANTEED

walgreens.com (c)2021 Walgreen Co.

MADE IN U.S.A. WITH U.S. AND FOREIGN COMPONENTS

PLASTIC BOTTLE

how2recycle.info

Principal display panel

Walgreens

Compare to the active ingredient in Listerine®Total Care Zero Anticavity Mouthwash††

WALGREENS PHARMACIST RECOMMENDED*

Alcohol Free

Anticavity Rinse

Mouthwash

SODIUM FLUORIDE 0.02% (0.01 W/V FLUORIDE ION) / ANTICAVITY

ALCOHOL FREE SUGAR FREE

- Helps strengthen teeth to fight cavities
- Restores enamel
- Kills bad breath germs

33.8 FL OZ (1.05 QT) 1 L

FRESH MINT flavor

IMPORTANT: Read directions for proper use